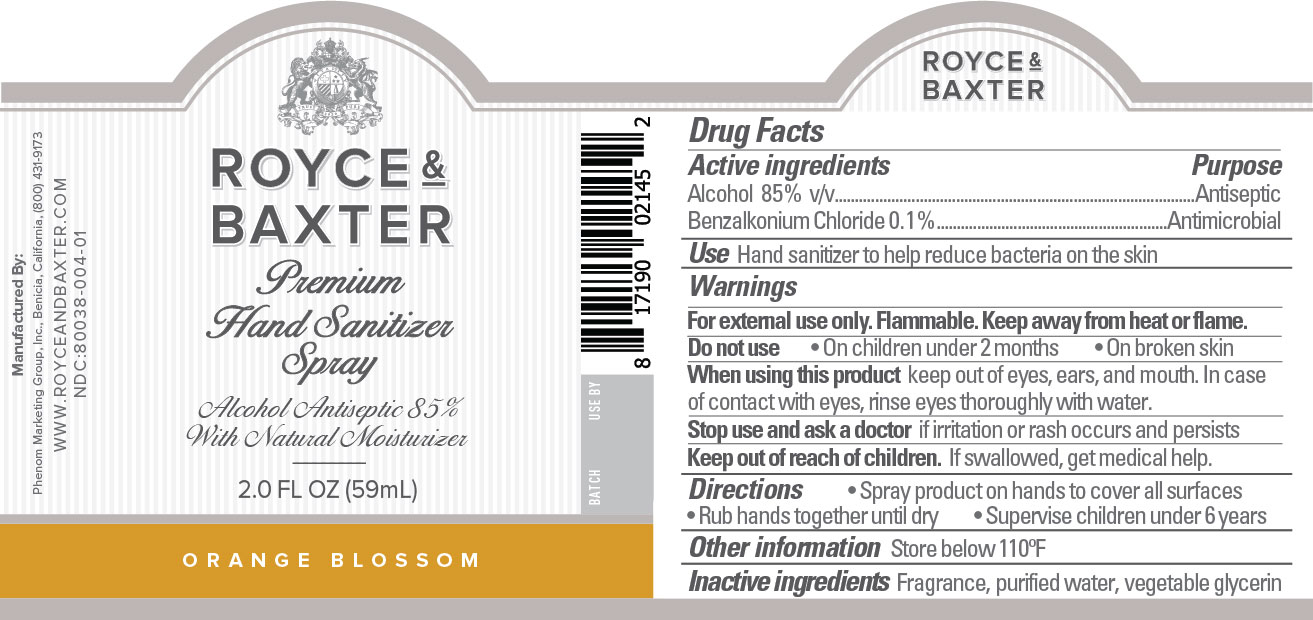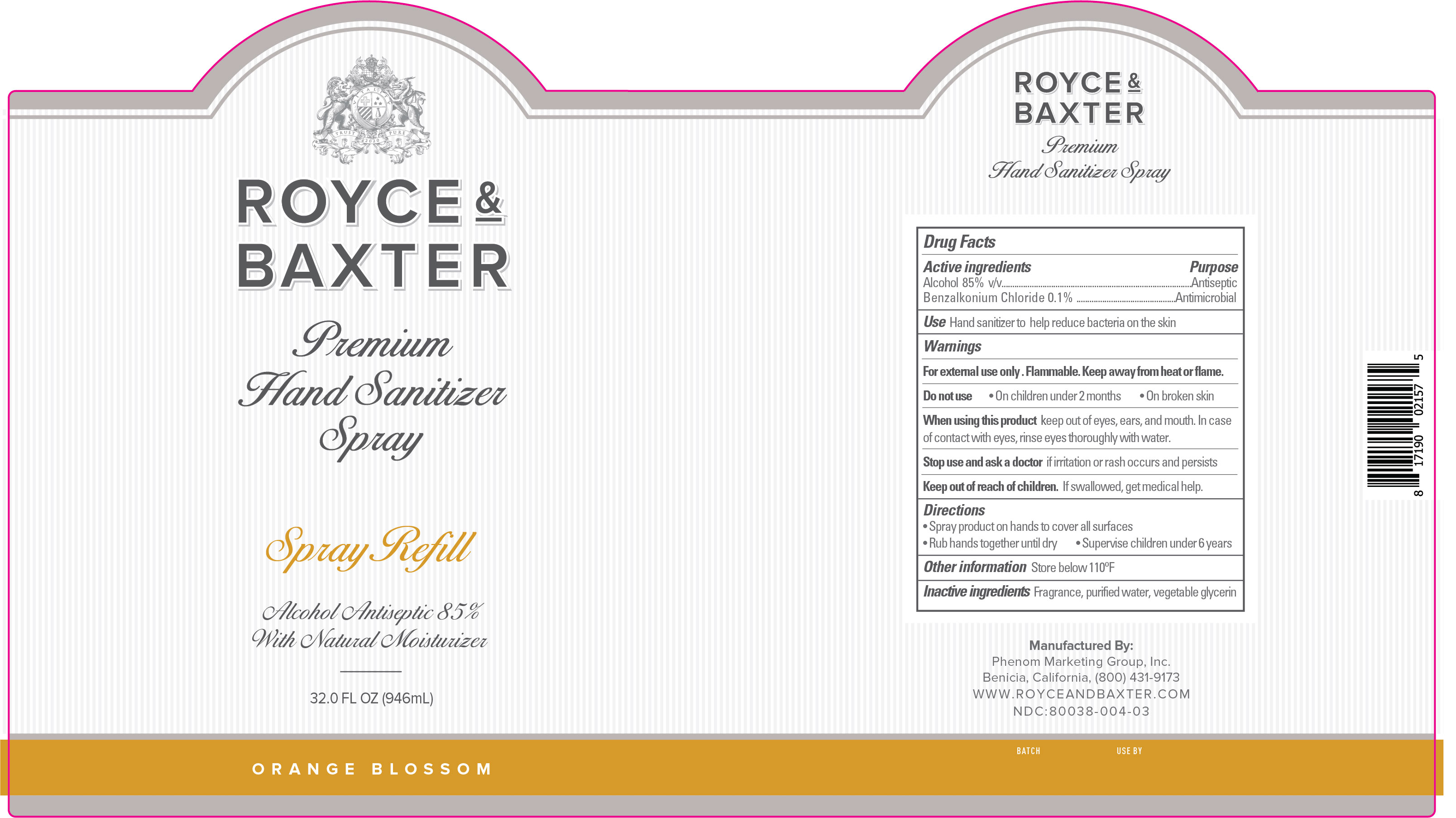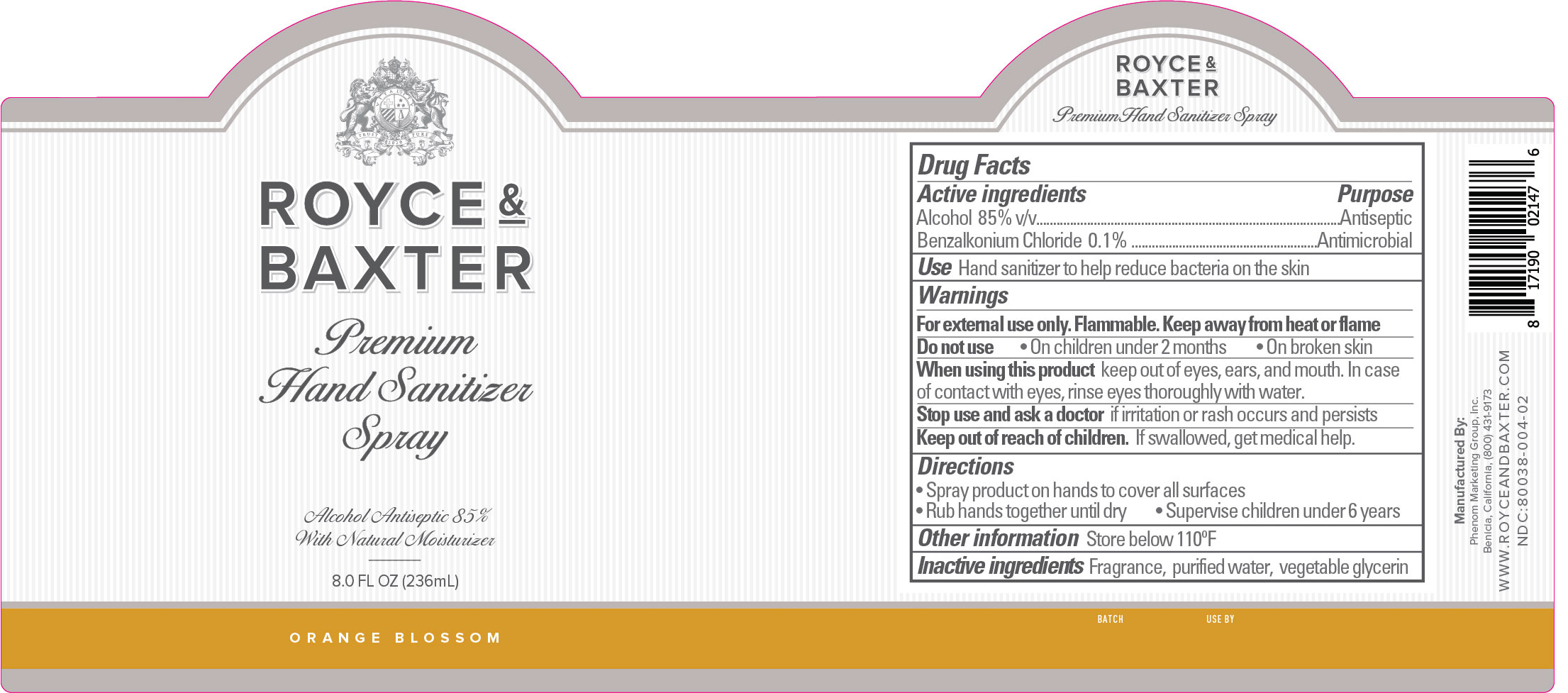 DRUG LABEL: Hand Sanitizer - Orange Blossom
NDC: 80038-004 | Form: LIQUID
Manufacturer: Phenom Marketing Group, Inc.
Category: otc | Type: HUMAN OTC DRUG LABEL
Date: 20220201

ACTIVE INGREDIENTS: BENZALKONIUM CHLORIDE 0.1 g/100 mL; ALCOHOL 85 mL/100 mL
INACTIVE INGREDIENTS: GLYCERIN 0.72 mL/100 mL; WATER

Active Ingredient(s)

Alcohol 85% v/v. Purpose: Antiseptic

Benzalkonium Chloride 0.1%. Purpose: Antimicrobial

Purpose

Antiseptic, Antimicrobial

Use

Hand Sanitizer to help reduce bacteria on the skin

Warnings

For external use only. Flammable. Keep away from heat or flame

Do not use

- On children under 2 months
- On broken skin

When using this product keep out of eyes, ears, and mouth. In case of contact with eyes, rinse eyes thoroughly with water.

Stop use and ask a doctor if irritation or rash occurs and persists

Keep out of reach of children. If swallowed, get medical help

Directions

- Spray product on hands to cover all surfaces
- Rub hands together until dry
- Supervise children under 6 years

Other information

Store below 110F

Inactive ingredients

Fragrance, purified water, vegetable glycerin

Package Label - Principal Display Panel

59 mL NDC: 80038-004-01

236 mL NDC: 80038-004-02

946 mL NDC: 80038-004-03